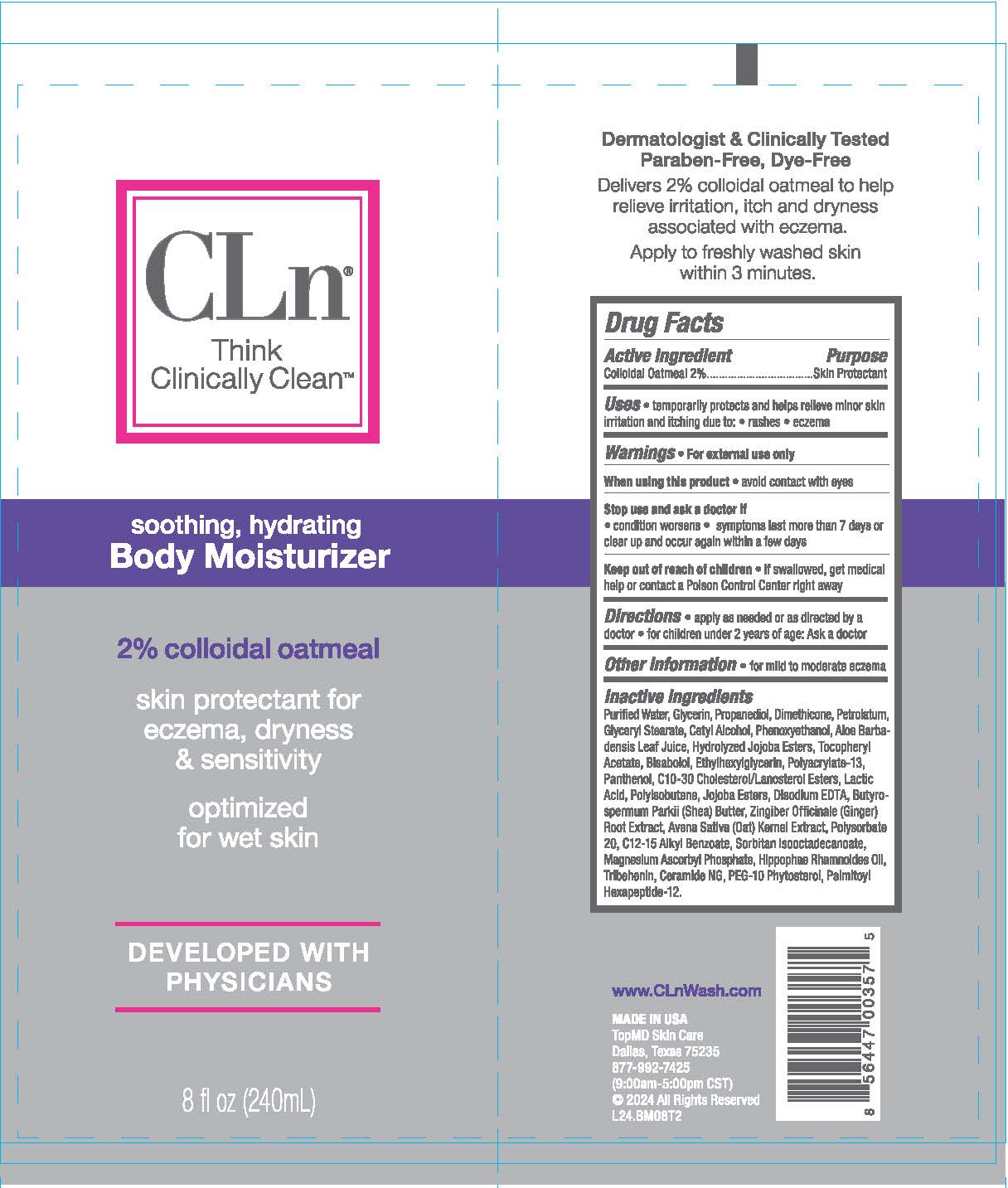 DRUG LABEL: CLn Body Moisturizer
NDC: 69530-858 | Form: CREAM
Manufacturer: TopMD Skin Care, Inc.
Category: otc | Type: HUMAN OTC DRUG LABEL
Date: 20250618

ACTIVE INGREDIENTS: OATMEAL 2 g/100 g
INACTIVE INGREDIENTS: LACTIC ACID; CERAMIDE NG; PALMITOYL HEXAPEPTIDE-12; PHENOXYETHANOL; BISABOLOL; POLYACRYLATE-13; PANTHENOL; GINGER; C12-15 ALKYL BENZOATE; GLYCERIN; ALOE VERA LEAF; CETYL ALCOHOL; BUTYROSPERMUM PARKII (SHEA) BUTTER; SORBITAN SESQUIISOSTEARATE; HIPPOPHAE RHAMNOIDES SEED OIL; TRIBEHENIN; DIMETHICONE; WATER; GLYCERYL STEARATE; ALPHA-TOCOPHEROL ACETATE; ETHYLHEXYLGLYCERIN; C10-30 CHOLESTEROL/LANOSTEROL ESTERS; HYDROLYZED JOJOBA ESTERS; PETROLATUM; EDETATE DISODIUM; MAGNESIUM ASCORBYL PHOSPHATE; POLYSORBATE 20; OAT; POLYISOBUTYLENE (1000 MW); PROPANEDIOL

CLn Body Moisturizer

Active Ingredients

2% Collodial Oatmeal

Purpose

Skin Protectant

Uses

Temporarily protects and helps releive minor skin irritation and itching due to: ● rashes ● ezcema

Warnings

For external use only.

When using this product

● avoid contact with eyes

Stop use and ask doctor if

● condition worsens ● symptoms last more than 7 days or clear up and occur again within a few days

Keep out of reach of children.

If swallowed, get medical help or contact a Poison Control Center right away.

Directions

● apply as needed or as directed by doctor ● for children under 2 years of age: Ask a doctor

Other Information

For mild to moderate ezcema

Inactive Ingredients

Water, Glycerin, Propanediol, Dimethicone, Petrolatum, Glyceryl Stearate, Cetyl Alcohol, Phenoxyethanol, Aloe Barbadensis Leaf Juice, Hydrolyzed Jojoba Esters, Tocopheryl Acetate, Bisabolol, Ethylhexylglycerin, Polyacrylate-13, Panthenol, C10-30 Cholesterol/Lanosterol Esters, Lactic Acid, Polyisobutene, Jojoba Esters, Disodium EDTA, Butyrospermum Parkii (Shea) Butter, Zingiber Officinale (Ginger) Root Extract, Avena Sativa (Oat) Kernel Extract, Polysorbate-20, C12-15 Alkyl Benzoate, Sorbitan Isooctadecanoate, Magnesium Ascorbyl Phosphate, Hippophae Ramnoides Oil, Tribenhenin, Ceramide NG, PEG-10 Phytosterol, Palmitoyl Hexapeptide-12